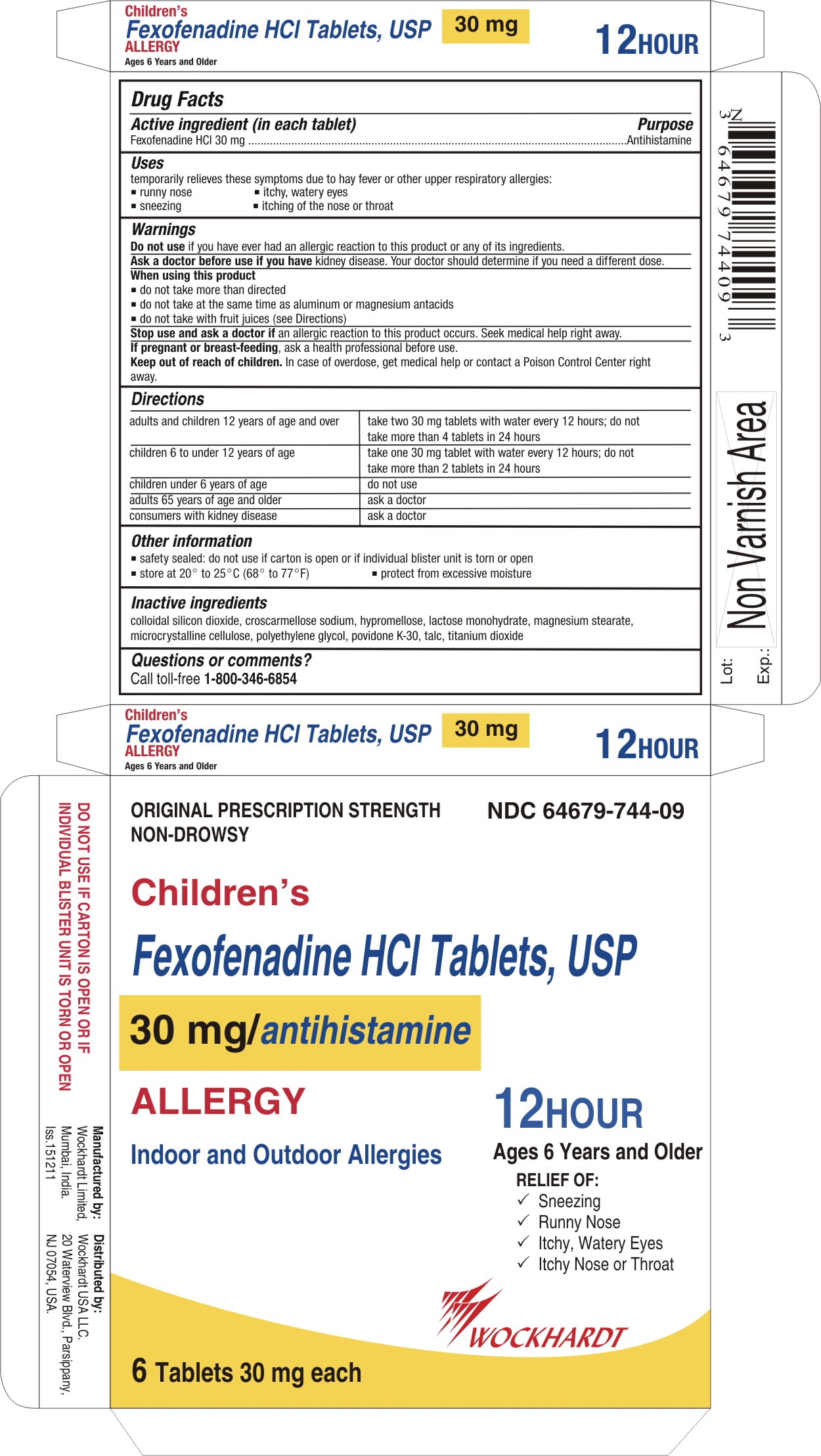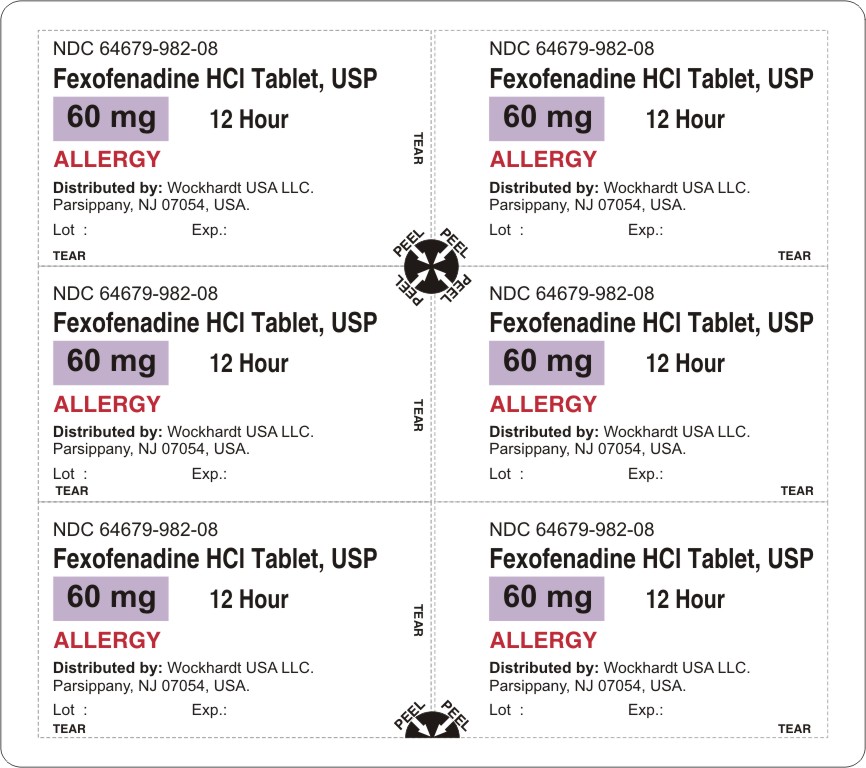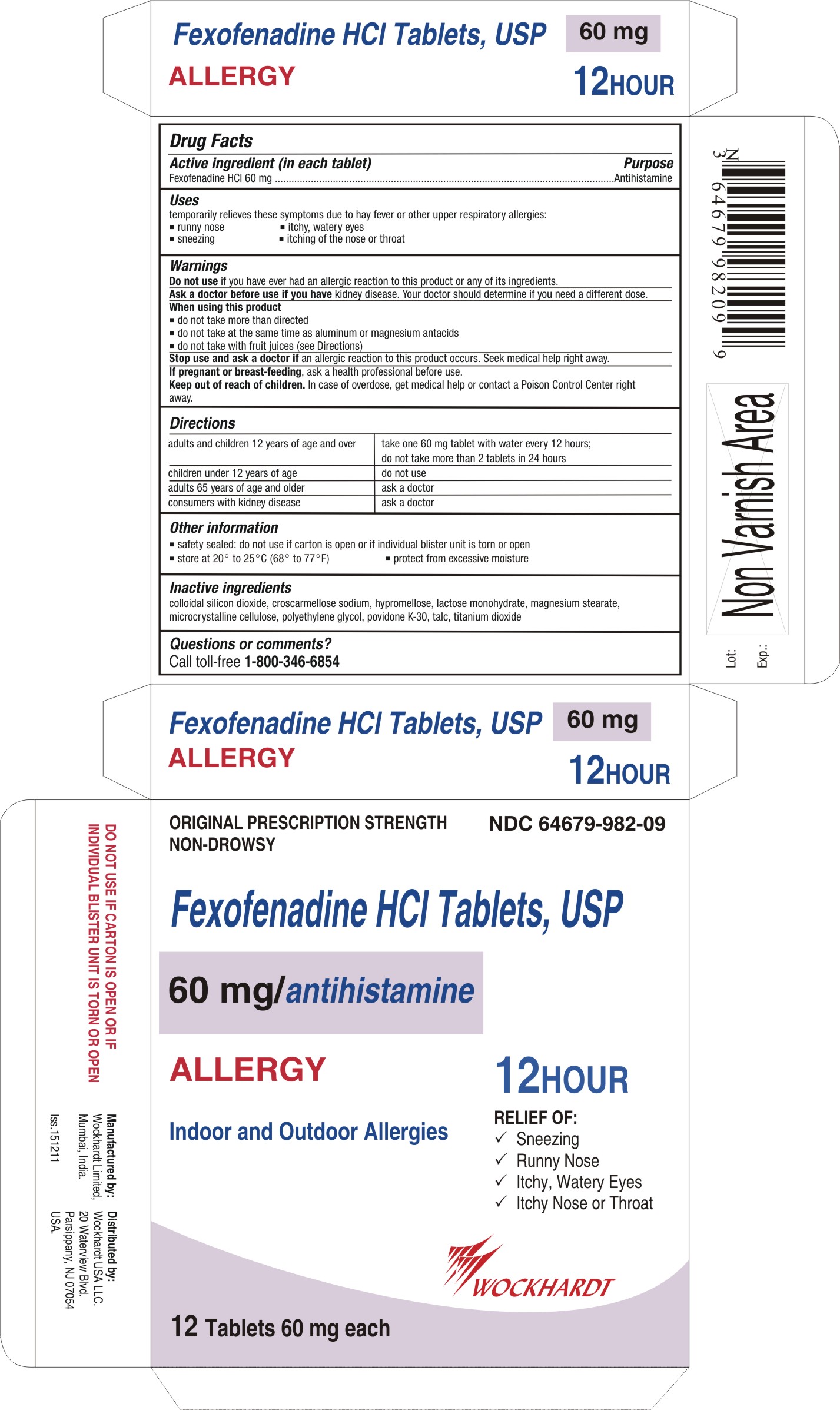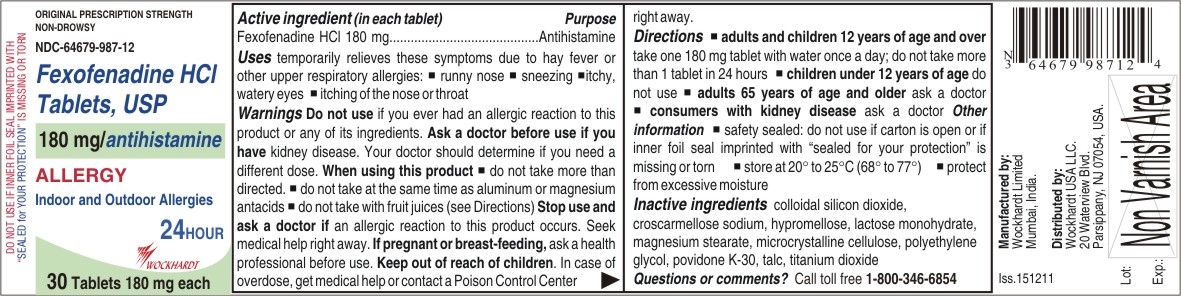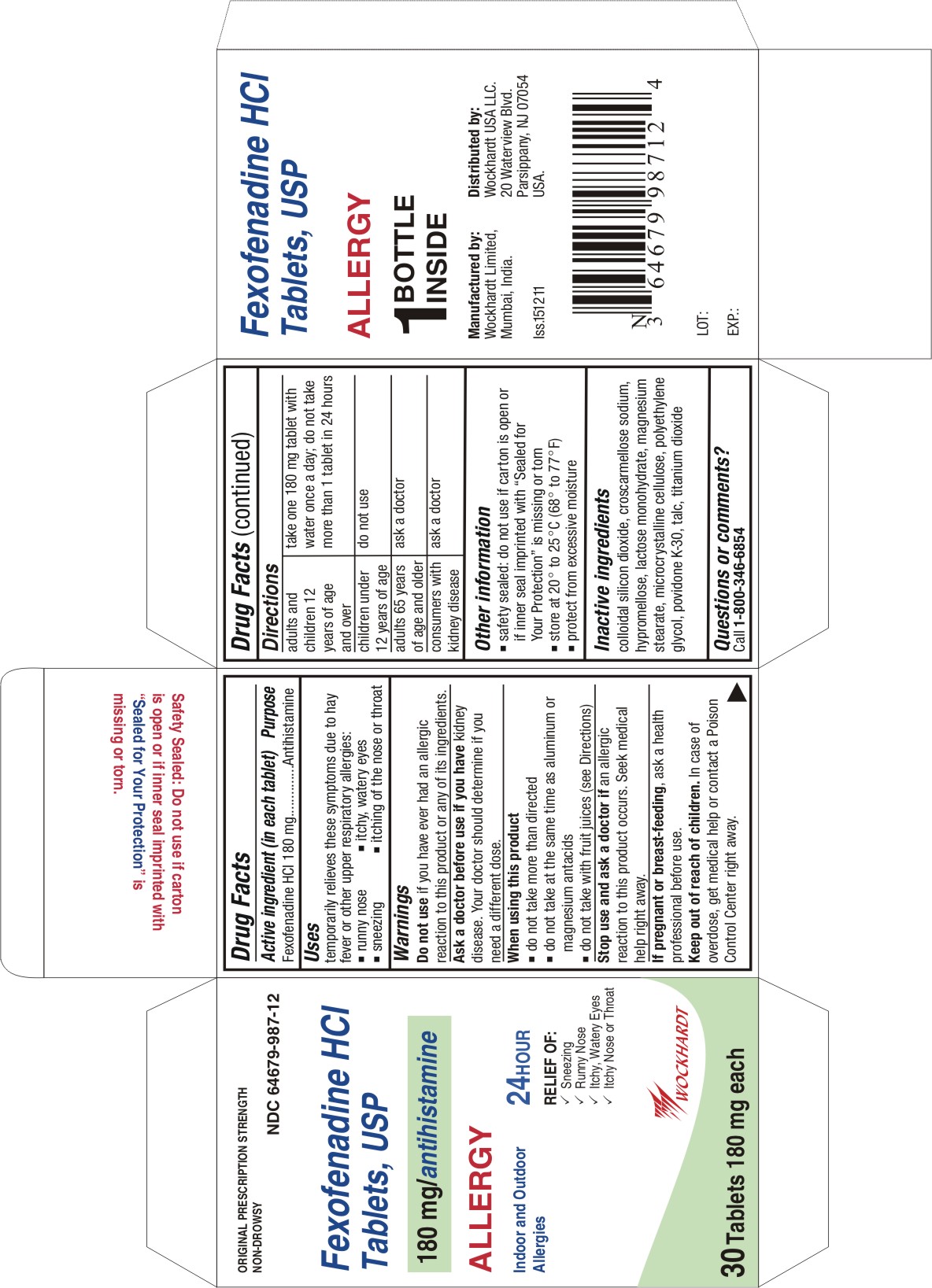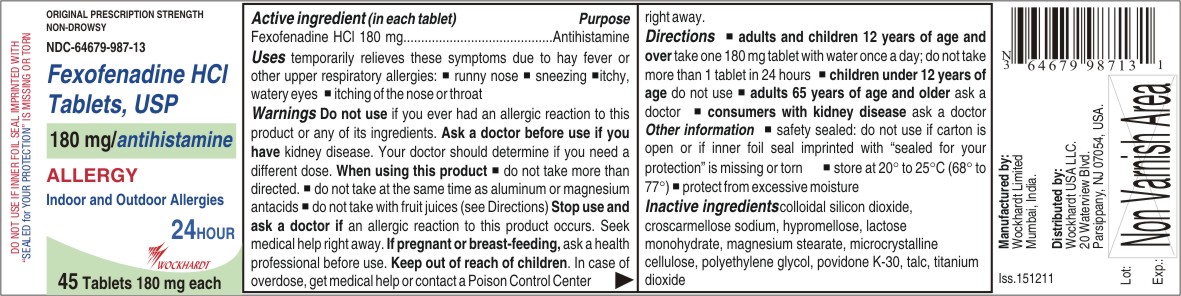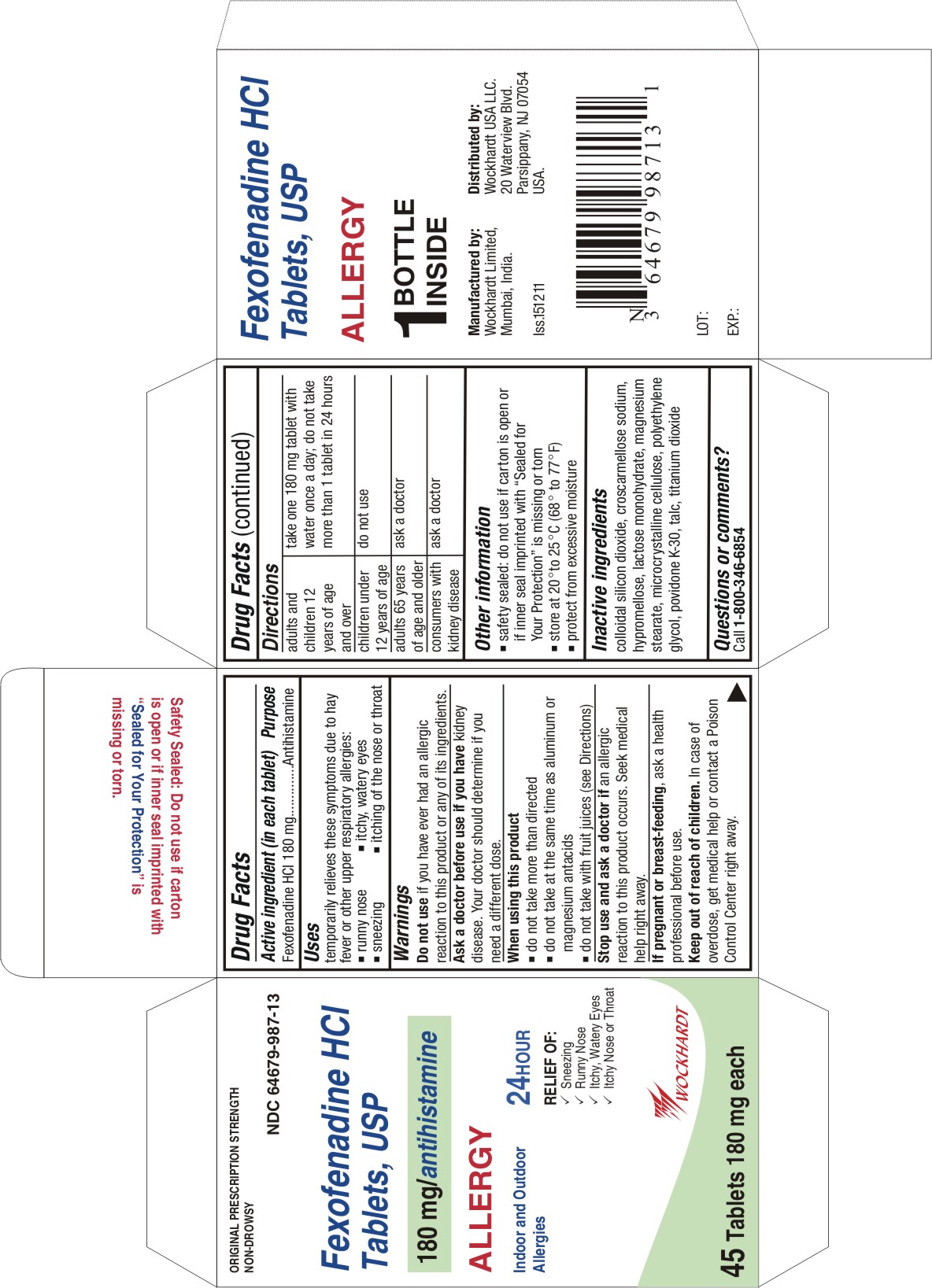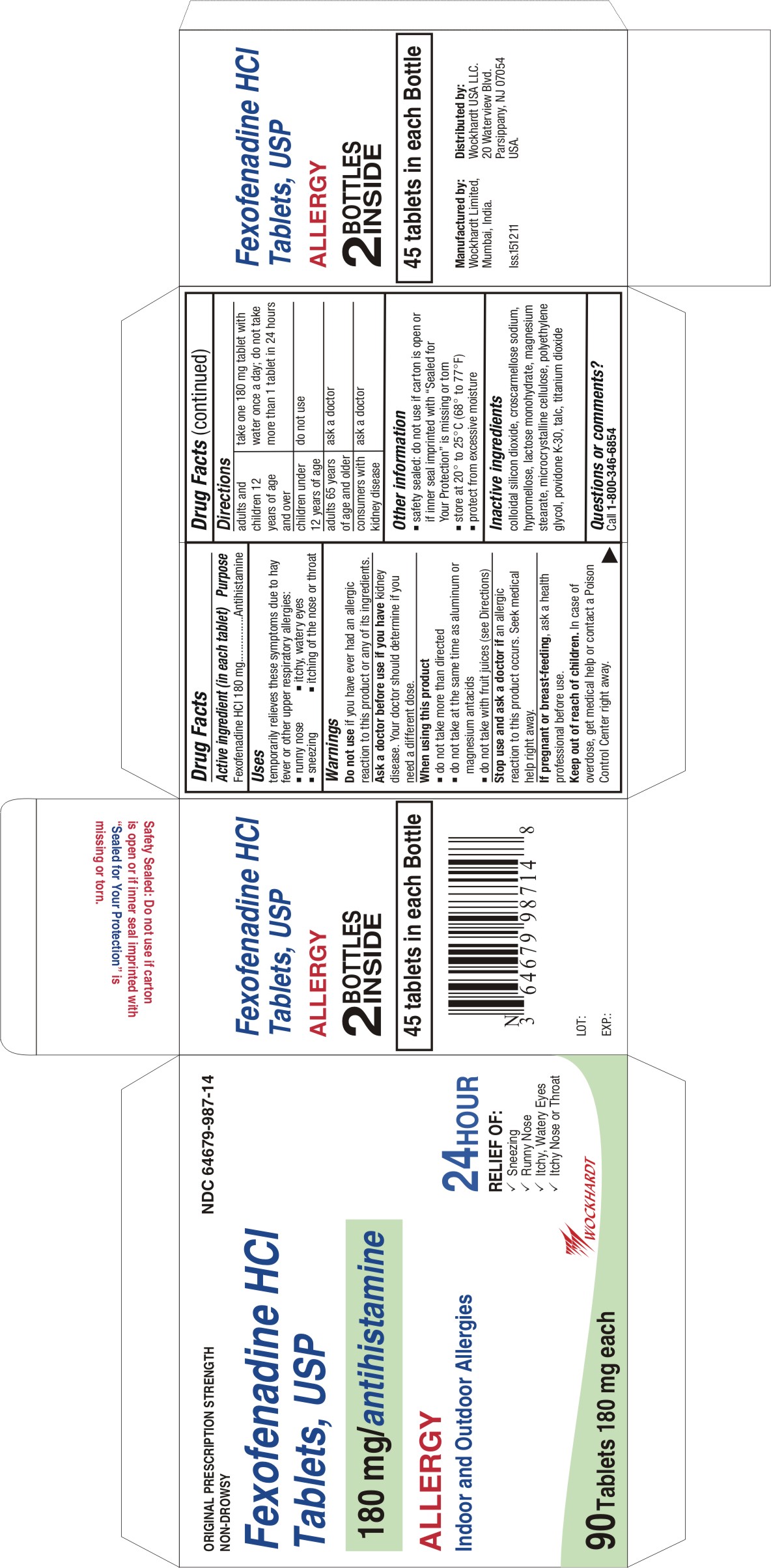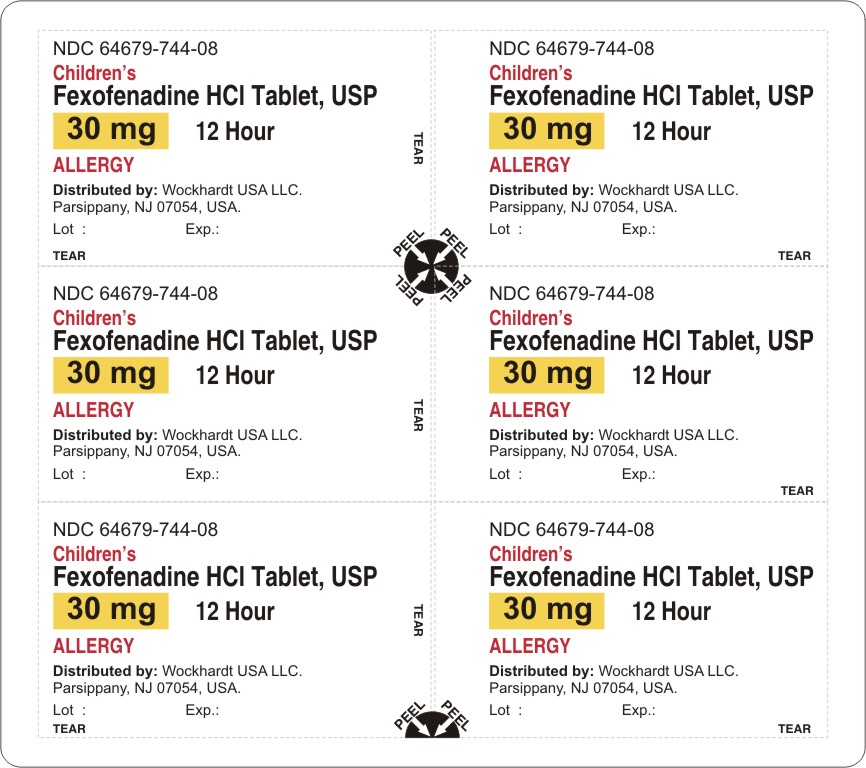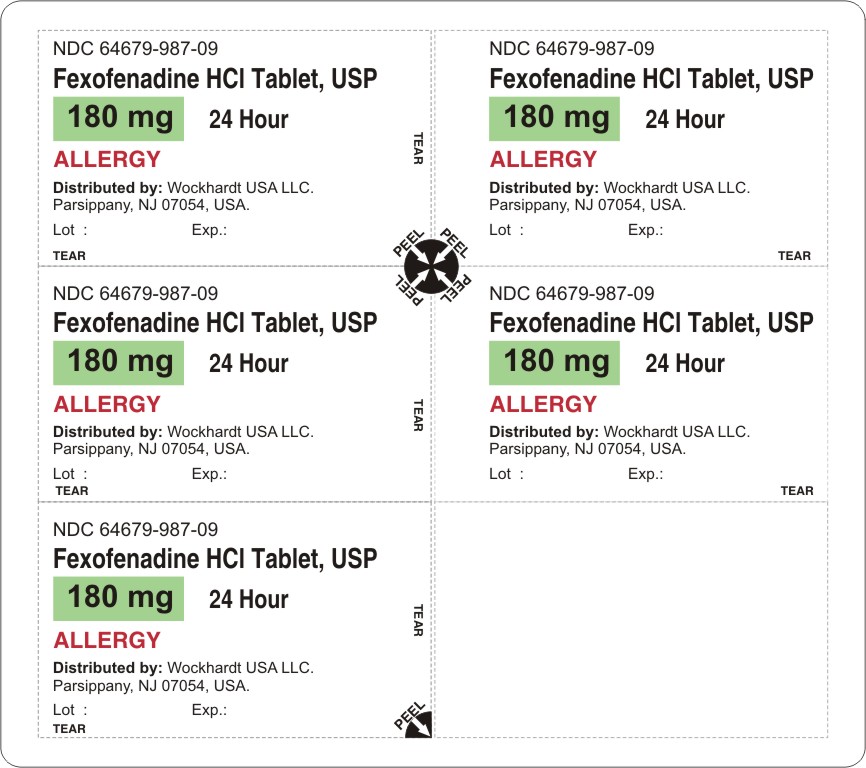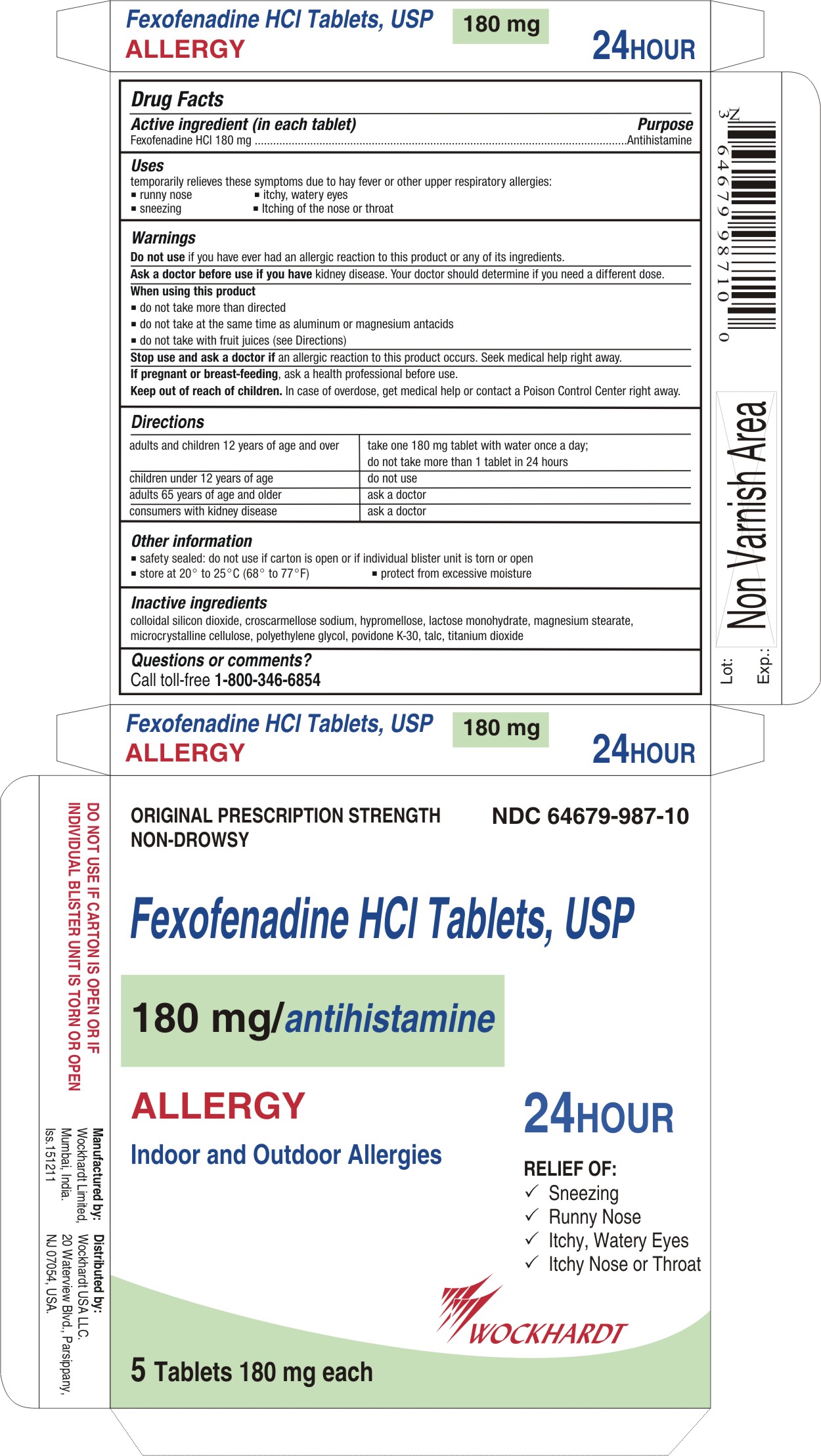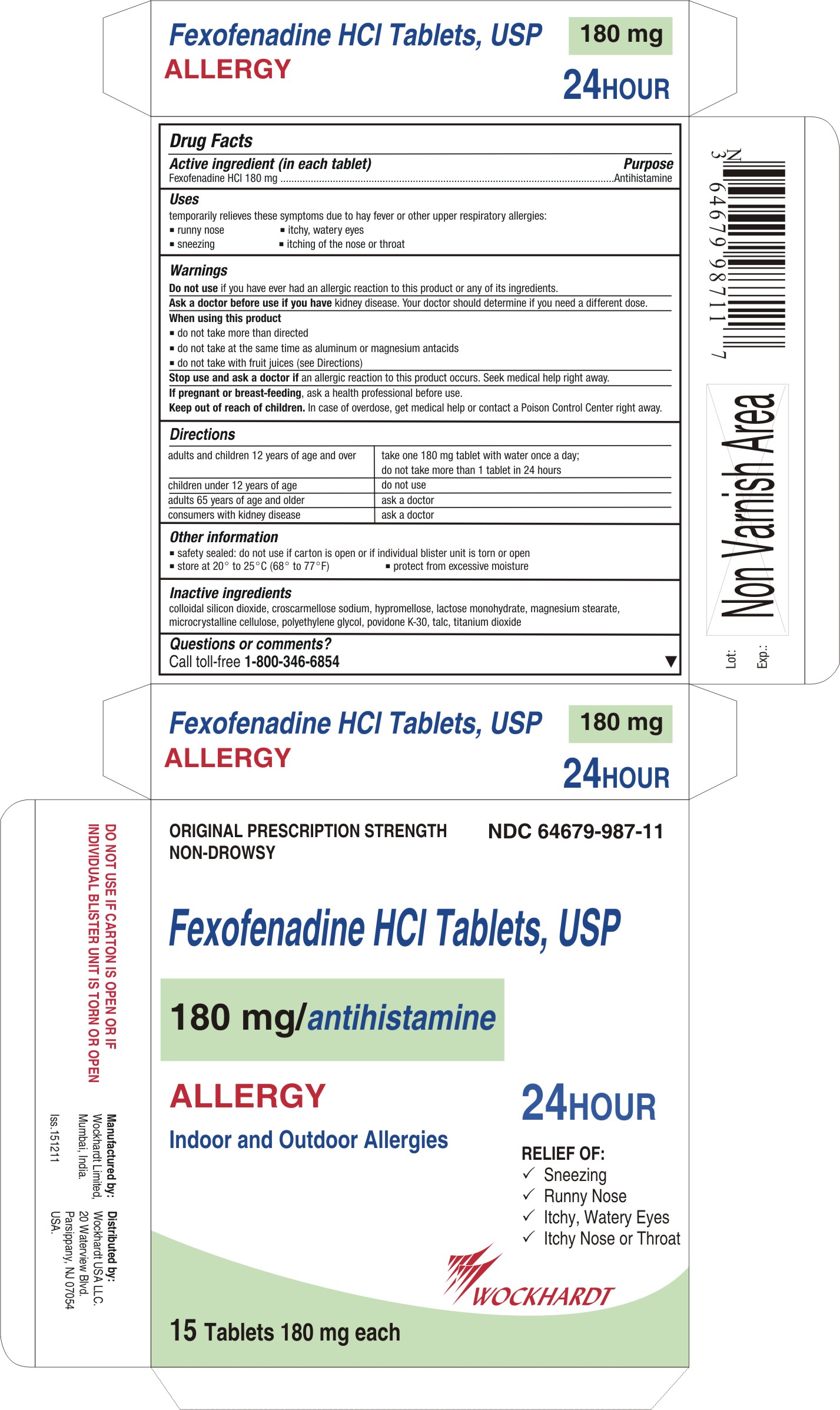 DRUG LABEL: Fexofenadine
NDC: 55648-744 | Form: TABLET, FILM COATED
Manufacturer: Wockhardt Limited
Category: otc | Type: HUMAN OTC DRUG LABEL
Date: 20120508

ACTIVE INGREDIENTS: FEXOFENADINE HYDROCHLORIDE 30 mg/1 1
INACTIVE INGREDIENTS: CELLULOSE, MICROCRYSTALLINE; CROSCARMELLOSE SODIUM; HYPROMELLOSES; LACTOSE MONOHYDRATE; MAGNESIUM STEARATE; POLYETHYLENE GLYCOLS; POVIDONE K30; SILICON DIOXIDE; TALC; TITANIUM DIOXIDE

Fexofenadine Tablets

Active ingredient (in each tablet)

For 30 mg:

Fexofenadine HCl 30 mg

For 60 mg:

Fexofenadine HCl 60 mg

For 180 mg:

Fexofenadine HCl 180 mg

Purpose

Antihistamine

Uses

temporarily relieves these symptoms due to hay fever or other upper respiratory allergies:

- runny nose
- sneezing
- itchy, watery eyes
- itching of the nose or throat

Warnings

Do not use

if you have ever had an allergic reaction to this product or any of its ingredients.

Ask a doctor before use if you have

kidney disease. Your doctor should determine if you need a different dose.

When using this product

- do not take more than directed
- do not take at the same time as aluminum or magnesium antacids
- do not take with fruit juices (see Directions)

Stop use and ask a doctor if

an allergic reaction to this product occurs. Seek medical help right away.

If pregnant or breast-feeding

ask a health professional before use.

Keep out of reach of children

In case of overdose, get medical help or contact a Poison Control Center right away.

Directions

For 30 mg:

adults and children 12 years of age and over | take two 30 mg tablets with water every 12 hours; do not take more than 4 tablets in 24 hours
children 6 to under 12 years of age | take one 30 mg tablet with water every 12 hours; do not take more than 2 tablets in 24 hours
children under 6 years of age | do not use
adults 65 years of age and older | ask a doctor
consumers with kidney disease | ask a doctor

For 60 mg:

adults and children 12 years of age and over | take one 60 mg tablet with water every 12 hours; do not take more than 2 tablets in 24 hours
children under 12 years of age | do not use
adults 65 years of age and older | ask a doctor
consumers with kidney disease | ask a doctor

For 180 mg:

adults and children 12 years of age and over | take one 180 mg tablet with water once a day; do not take more than 1 tablet in 24 hours
children under 12 years of age | do not use
adults 65 years of age and older | ask a doctor
consumers with kidney disease | ask a doctor

Other information

- safety sealed: do not use if carton is open or if inner seal imprinted with "Sealed for Your Protection" is missing or torn
- safety sealed: do not use if carton is open or if individual blister unit is torn or open
- store between 20° to 25°C (68° to 77°F)
- protect from excessive moisture

Inactive ingredients

colloidal silicon dioxide, croscarmellose sodium, hypromellose, lactose monohydrate, magnesium stearate, microcrystalline cellulose, polyethylene glycol, povidone K-30, talc, titanium dioxide

Questions or comments?

Call toll-free 1-800-346-6854